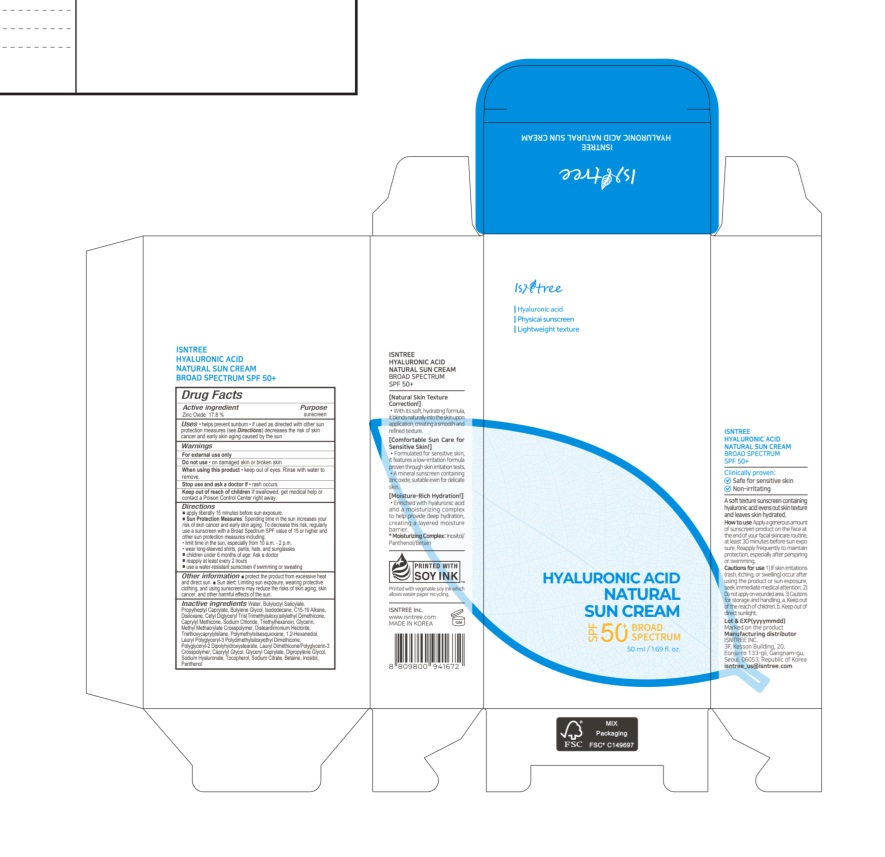 DRUG LABEL: ISNTREE HYALURONIC ACID NATURAL SUNCREAM
NDC: 81100-504 | Form: CREAM
Manufacturer: ISNTREE Inc.
Category: otc | Type: HUMAN OTC DRUG LABEL
Date: 20250323

ACTIVE INGREDIENTS: ZINC OXIDE 8.9 g/50 mL
INACTIVE INGREDIENTS: ISODODECANE; DISILOXANE; CAPRYLYL METHICONE; PANTHENOL; C15-19 ALKANE; POLYMETHYLSILSESQUIOXANE (4.5 MICRONS); CAPRYLYL GLYCOL; GLYCERYL CAPRYLATE; SODIUM HYALURONATE; INOSITOL; 1,2-HEXANEDIOL; TOCOPHEROL; TRIETHOXYCAPRYLYLSILANE; DIPROPYLENE GLYCOL; SODIUM CITRATE; WATER; BETAINE; PROPYLHEPTYL CAPRYLATE; BUTYLOCTYL SALICYLATE; BUTYLENE GLYCOL; SODIUM CHLORIDE; CETYL DIGLYCERYL TRIS(TRIMETHYLSILOXY)SILYLETHYL DIMETHICONE (3500 MM2/S); TRIETHYLHEXANOIN; GLYCERIN; POLYGLYCERYL-2 DIPOLYHYDROXYSTEARATE; DISTEARDIMONIUM HECTORITE; LAURYL POLYGLYCERYL-3 POLYDIMETHYLSILOXYETHYL DIMETHICONE (4000 MPA.S)

ISNTREE HYALURONIC ACID NATURAL SUN CREAM

Active ingredient

Zinc Oxide 17.8 %

Purpose

sunscreen

Uses

• helps prevent sunburn • higher SPF gives more sunburn protection
• if used as directed with other sun protection measures (see Directions)
decreases the risk of skin cancer and early skin aging caused by the sun

Warnings

For external use only.

Do not use

• on damaged skin or broken skin.

When using this product

• keep out of eyes. Rinse with water to remove.

Stop use and ask a doctor if

•rash or irritation develops and lasts.

Keep out of reach of children

If swallowed, get medical help or contact
a Poison Control Center right away.

Directions

■ apply liberally 15 minutes before sun exposure.
Sun Protection Measures. Spending time in the sun increases your risk of
skin cancer and early skin aging. To decrease this risk, regularly use a
sunscreen with a Broad Spectrum SPF value of 15 or higher and other
sun protection measures including:
• limit time in the sun, especially from 10 a.m. - 2 p.m.
• wear long-sleeved shirts, pants, hats, and sunglasses
■ children under 6 months of age: Ask a doctor
■ reapply at least every 2 hours.
■ use a water-resistant sunscreen if swimming or sweating.

Other information

■ protect the product from excessive heat and
direct sun ■ Sun alert: Limiting sun exposure, wearing protective clothing, and
using sunscreens may reduce the risks of skin aging, skin cancer, and other
harmful effects of the sun.

Inactive ingredients

Water, Butyloctyl Salicylate, Propylheptyl Caprylate, Butylene Glycol, Isododecane, C15-19 Alkane, Disiloxane, Cetyl Diglyceryl Tris(Trimethylsiloxy)silylethyl Dimethicone, Caprylyl Methicone, Sodium Chloride, Triethylhexanoin, Glycerin, Methyl Methacrylate Crosspolymer, Disteardimonium Hectorite, Triethoxycaprylylsilane, Polymethylsilsesquioxane, 1,2-Hexanediol, Lauryl Polyglyceryl-3 Polydimethylsiloxyethyl Dimethicone, Polyglyceryl-2 Dipolyhydroxystearate, Lauryl Dimethicone/Polyglycerin-3 Crosspolymer, Caprylyl Glycol, Glyceryl Caprylate, Dipropylene Glycol, Sodium Hyaluronate, Tocopherol, Sodium Citrate, Betaine, Inositol, Panthenol